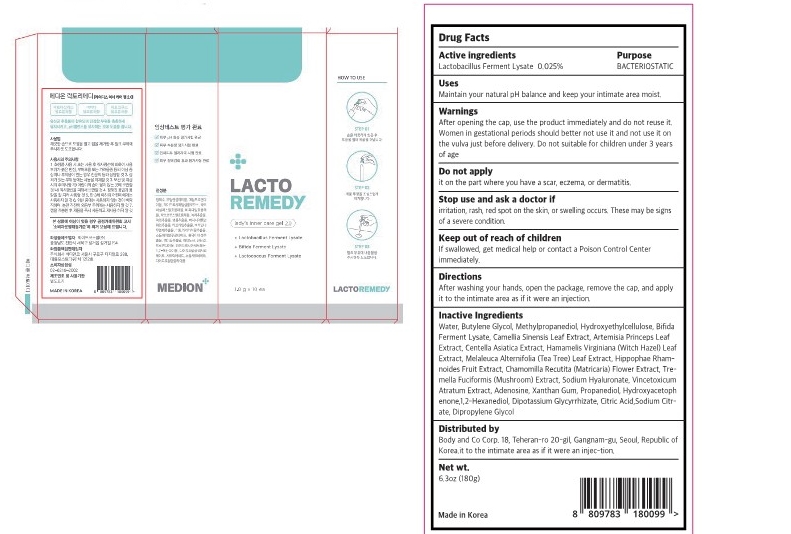 DRUG LABEL: LACTO REMEDY Ladys inner care gel
NDC: 83490-304 | Form: SOLUTION, GEL FORMING / DROPS
Manufacturer: 2359 US INC
Category: otc | Type: HUMAN OTC DRUG LABEL
Date: 20230524

ACTIVE INGREDIENTS: LIMOSILACTOBACILLUS FERMENTUM 0.025 g/100 g
INACTIVE INGREDIENTS: METHYLPROPANEDIOL; HYDROXYETHYL CELLULOSE, UNSPECIFIED; MELALEUCA ALTERNIFOLIA LEAF; WATER; CENTELLA ASIATICA TRITERPENOIDS; CHAMOMILE; HYALURONATE SODIUM; PROPANEDIOL; DIPROPYLENE GLYCOL; BUTYLENE GLYCOL; ARTEMISIA PRINCEPS LEAF; ADENOSINE; 1,2-HEXANEDIOL; HAMAMELIS VIRGINIANA LEAF; GREEN TEA LEAF; HIPPOPHAE RHAMNOIDES FRUIT; TREMELLA FUCIFORMIS WHOLE; VINCETOXICUM ATRATUM WHOLE; XANTHAN GUM; HYDROXYACETOPHENONE; GLYCYRRHIZINATE DIPOTASSIUM; ACONITIC ACID; SODIUM CITRATE

LACTO REMEDY Lady's inner care gel 82892-304

Active Ingredients

Lactobacillus Ferment Lysate

Purpose

BACTERIOSTATIC

use

Maintain your natural pH balance and keep your intimate area moist.

warnings

Do not use it on the part where you have a scar, eczema, or dermatitis.

Do not suitable for children under 3 years of age

warnings

After opening the cap, use the product immediately and do not reuse it. Women in gestational periods should better not use it and not use it on the vulva just before delivery.

warnings

Stop use and ask a doctor if
irritation, rash, red spot on the skin, or swelling occurs. These may be signs of a severe condition.

warnings

After opening the cap, use the product immediately and do not reuse it.

warnings

Keep out of reach of children
If swallowed, get medical help or contact a Poison Control Center immediately.

Directions

After washing your hands, open the package, remove the cap, and apply it to the intimate area as if it were an injection.

Inactive Ingredients

Water, Butylene Glycol, Methylpropanediol, Hydroxyethylcellulose, Bifida Ferment Lysate, Camellia Sinensis Leaf Extract, Artemisia Princeps Leaf Extract, Centella Asiatica Extract, Hamamelis Virginiana (Witch Hazel) Leaf Extract, Melaleuca Alternifolia (Tea Tree) Leaf Extract, Hippophae Rham- noides Fruit Extract, Chamomilla Recutita (Matricaria) Flower Extract, Tre- mella Fuciformis (Mushroom) Extract, Sodium Hyaluronate, Vincetoxicum Atratum Extract, Adenosine, Xanthan Gum, Propanediol, Hydroxyacetoph enone,1,2-Hexanediol, Dipotassium Glycyrrhizate, Citric Acid,Sodium Citr- ate, Dipropylene Glycol

label